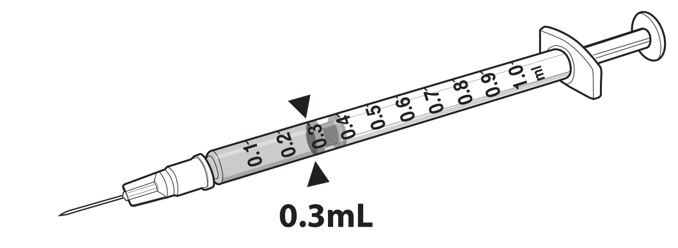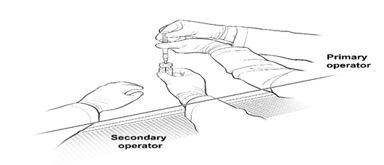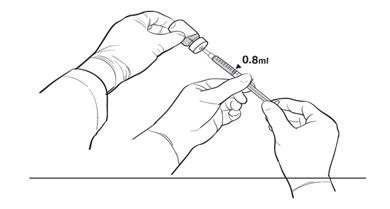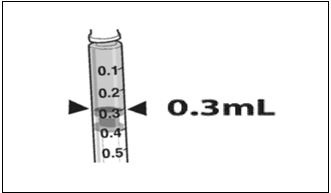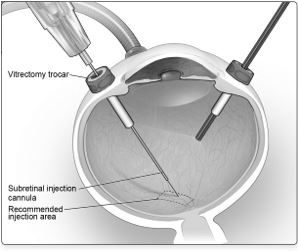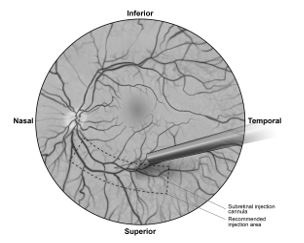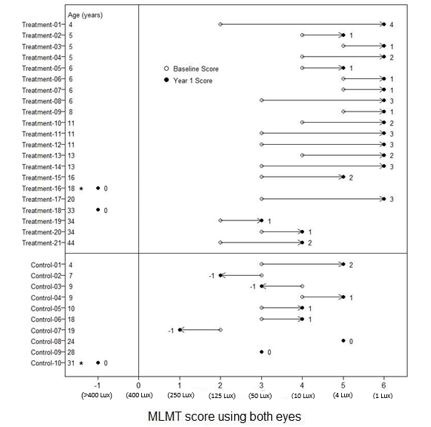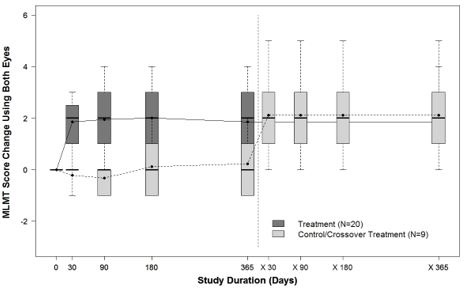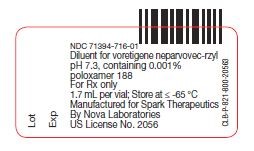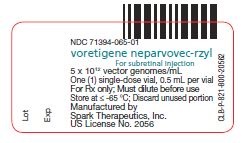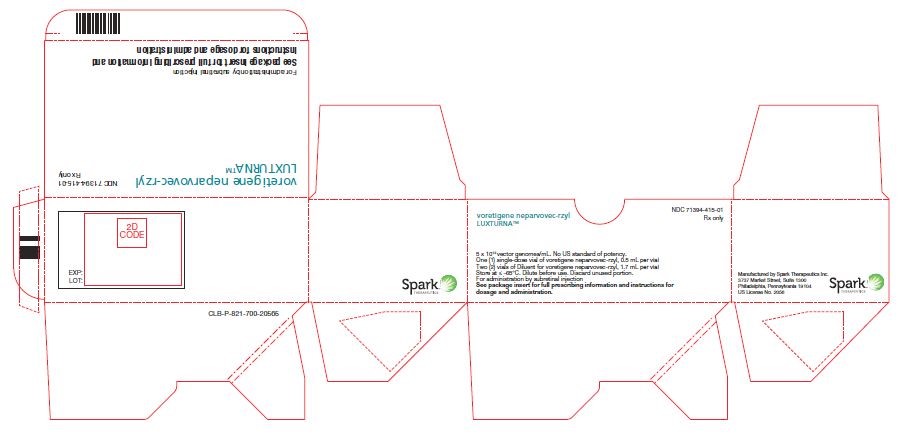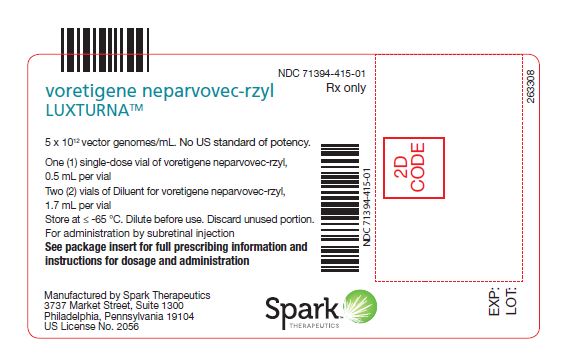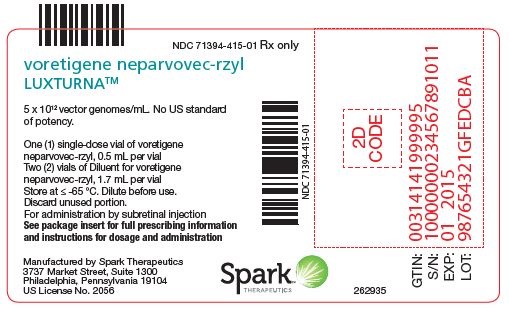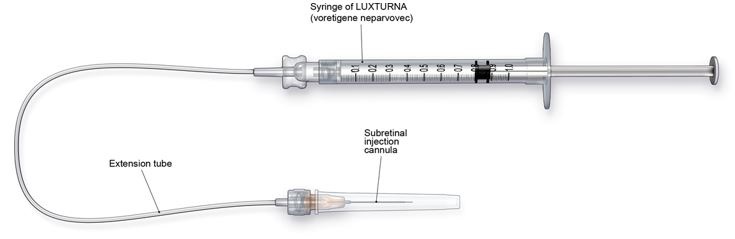 DRUG LABEL: LUXTURNA
NDC: 71394-415 | Form: KIT | Route: SUBRETINAL
Manufacturer: Spark Therapeutics, Inc.
Category: prescription | Type: HUMAN PRESCRIPTION DRUG LABEL
Date: 20220501

ACTIVE INGREDIENTS: VORETIGENE NEPARVOVEC 0.05 mg/1 1
INACTIVE INGREDIENTS: SODIUM PHOSPHATE, MONOBASIC, MONOHYDRATE 2.3 mmol/1 1; SODIUM PHOSPHATE, DIBASIC, DIHYDRATE 7.7 mmol/1 1; SODIUM CHLORIDE 180 mmol/1 1; POLOXAMER 188 0.001 1/1 1; WATER; SODIUM PHOSPHATE, MONOBASIC, UNSPECIFIED FORM 2.3 mmol/1 1; SODIUM PHOSPHATE, DIBASIC, UNSPECIFIED FORM 7.7 mmol/1 1; SODIUM CHLORIDE 180 mmol/1 1; POLOXAMER 188 0.001 1/1 1; WATER

HIGHLIGHTS OF PRESCRIBING INFORMATION

These highlights do not include all the information needed to use LUXTURNA safely and effectively. See full prescribing information for LUXTURNA.
LUXTURNA (voretigene neparvovec-rzyl) intraocular suspension for subretinal injection
Initial U.S. Approval: 2017

1 INDICATIONS AND USAGE

LUXTURNA is an adeno-associated virus vector-based gene therapy indicated for the treatment of patients with confirmed biallelic RPE65 mutation-associated retinal dystrophy. Patients must have viable retinal cells as determined by the treating physician(s). (1)

2 DOSAGE AND ADMINISTRATION

For subretinal injection only.

- The recommended dose of LUXTURNA for each eye is 1.5 x 10^11 vector genomes (vg), administered by subretinal injection in a total volume of 0.3 mL. (2.1)
- Perform subretinal administration of LUXTURNA to each eye on separate days within a close interval, but no fewer than 6 days apart. (2.1)
- Recommend systemic oral corticosteroids equivalent to prednisone at 1 mg/kg/day (maximum of 40 mg/day) for a total of 7 days (starting 3 days before administration of LUXTURNA to each eye), and followed by a tapering dose during the next 10 days. (2.1)

3 DOSAGE FORMS AND STRENGTHS

LUXTURNA is a suspension for subretinal injection, supplied in a 0.5 mL extractable volume in a single-dose 2 mL vial for a single administration in one eye. The supplied concentration (5 x 10^12vg/mL) requires a 1:10 dilution prior to administration. The Diluent is supplied in two single-use 2-mL vials. (3)

4 CONTRAINDICATIONS

None.

5 WARNINGS AND PRECAUTIONS

- Endophthalmitis: Use proper aseptic injection technique and monitor for signs and symptoms of infection. (5.1)
- Permanent decline in visual acuity: Monitor for visual disturbances. (5.2)
- Retinal abnormalities: Monitor for macular abnormalities, retinal tears or breaks and chorioretinal atrophy. Do not inject in the immediate vicinity of the fovea. (5.3)
- Increased intraocular pressure: Monitor and manage intraocular pressure elevations. (5.4)
- Expansion of intraocular air bubbles: Air travel and/or scuba diving is not recommended until any intraocular air bubbles have been absorbed. (5.5)
- Cataract: Subretinal injection of LUXTURNA may result in cataract formation or increase in the rate of cataract progression. (5.6)

6 ADVERSE REACTIONS

The most common adverse reactions (incidence ≥ 5%) in the clinical trials were conjunctival hyperemia, cataract, increased intraocular pressure, retinal tear, dellen (thinning of the corneal stroma), macular hole, subretinal deposits, eye inflammation, eye irritation, eye pain, and maculopathy (wrinkling on the surface of the macula). (6)

To report SUSPECTED ADVERSE REACTIONS, contact Spark Therapeutics, Inc. at 1-855-SPARKTX, or FDA at 1-800-FDA-1088 or www.fda.gov/medwatch.

8 USE IN SPECIFIC POPULATIONS

Pediatric use: Use in infants under 12 months of age is not recommended because of potential dilution or loss of LUXTURNA after administration due to the active retinal cell proliferation occurring in this age group. (8.4)

FULL PRESCRIBING INFORMATION

1 INDICATIONS AND USAGE

LUXTURNA (voretigene neparvovec-rzyl) is an adeno-associated virus vector-based gene therapy indicated for the treatment of patients with confirmed biallelic RPE65 mutation-associated retinal dystrophy.

Patients must have viable retinal cells as determined by the treating physician(s).

2 DOSAGE AND ADMINISTRATION

For subretinal injection only.

2.1 Dose

- The recommended dose of LUXTURNA for each eye is 1.5 x 10^11 vector genomes (vg), administered by subretinal injection in a total volume of 0.3 mL.
- Perform subretinal administration of LUXTURNA to each eye on separate days within a close interval, but no fewer than 6 days apart.
- Recommend systemic oral corticosteroids equivalent to prednisone at 1 mg/kg/day (maximum of 40 mg/day) for a total of 7 days (starting 3 days before administration of LUXTURNA to the first eye), and followed by tapering the dose during the following 10 days. The same corticosteroid dosing regimen applies for the administration of LUXTURNA to the second eye. If the corticosteroid taper following LUXTURNA administration to the first eye is not complete three days prior to the planned LUXTURNA administration to the second eye, then the corticosteroid regimen for the second eye replaces the taper for the first eye.

2.2 Preparation

Prepare LUXTURNA within 4 hours of administration using sterile technique under aseptic conditions in a Class II vertical laminar flow biological safety cabinet (BSC). Below is the list of items required for dilution and administration syringe preparation:

- One single-dose vial of LUXTURNA
- Two vials of Diluent
- One 3-mL sterile syringe
- One 20G 1-inch sterile needle
- Three 1-mL sterile syringes
- Three 27G ½-inch sterile needles
- Two sterile syringe caps
- One 10-mL sterile empty glass vial
- One sterile utility drape
- One sterile plastic bag
- Two sterile labels for administration syringes
- One sterile plain label
- One sterile skin marker

Dilution of LUXTURNA

1. Thaw one single-dose vial of LUXTURNA and two vials of Diluent at room temperature.
2. Mix the contents of the thawed Diluent vials by gently inverting them approximately 5 times.
3. Inspect the Diluent vials. If particulates, cloudiness, or discoloration are visible, do not use the vial(s); new vial(s) of Diluent should be used.
4. Obtain a 3-mL sterile syringe, a 20G 1-inch sterile needle, and a 10-mL sterile empty glass vial.
5. Using the 3-mL syringe with 20G 1-inch needle, transfer 2.7 mL of Diluent to the 10-mL glass vial. Dispose of the needle and syringe in an appropriate container.
6. Mix the contents of the thawed LUXTURNA single-dose vial by gently inverting approximately 5 times.
7. Inspect the LUXTURNA single-dose vial. If particulates, cloudiness, or discoloration are visible, do not use the vial; a new single-dose vial of LUXTURNA should be used.
8. Draw 0.3 mL of LUXTURNA into a 1-mL sterile syringe with a 27G ½-inch sterile needle. (Figure 1)

Figure 1. Syringe with 0.3 mL LUXTURNA

9. Transfer 0.3 mL of LUXTURNA to the glass vial containing 2.7 mL of Diluent from Step 5. Gently invert the 10-mL glass vial approximately 5 times to mix the contents.

10. Using the sterile plain label and sterile skin marker, label the 10-mL glass vial containing the diluted LUXTURNA as follows: "Diluted LUXTURNA".
11. Remove all items from the BSC except the glass vial labeled 'Diluted LUXTURNA' and the sterile skin marker.
12. Re-sanitize the BSC prior to the next steps and place the glass vial and the sterile marker to the left side in the BSC.

Preparation of LUXTURNA for Injection

To keep the syringes sterile, two operators are required for transfer of the contents of the 10-mL glass vial labeled 'Diluted LUXTURNA' into each of two sterile 1-mL syringes.

13. Place a sterile utility drape, a sterile plastic bag, and two sterile labels into the BSC.
14. Place the sterile drape near the Primary Operator on the right side of the sanitized BSC surface, away from the diluted LUXTURNA.
15. The Secondary Operator unwraps two 1-mL syringes, two 27G ½-inch needles, and two syringe caps in the BSC, ensuring that the Primary Operator touches only sterile surfaces while transferring the items onto the sterile drape.
16. The Secondary Operator changes to a new pair of sterile gloves and stands or sits to the left of the Primary Operator. The Secondary Operator holds the 10-mL glass vial containing the diluted LUXTURNA (Figure 2a).

Figure 2a. First Position of the Operators During Preparation of LUXTURNA Syringes

17. The Primary Operator withdraws 0.8 mL of the diluted LUXTURNA into a sterile 1-mL syringe using a 27G ½-inch sterile needle while the secondary operator holds the 10-mL glass vial. After the insertion of the needle, the Secondary Operator inverts the 10-mL glass vial enabling the Primary Operator to withdraw 0.8 mL without touching the 10-mL glass vial (Figure 2b).

Figure 2b. Second Position of the Operators During Preparation of LUXTURNA Syringes

18. The Primary Operator removes the needle and affixes a sterile cap to the sterile syringe, disposes of the needle in an appropriate container, and attaches a sterile label to the administration syringe.

19. The Primary Operator repeats Steps 17 and 18 to prepare a total of two administration syringes. Label the first syringe "Diluted LUXTURNA" and label the second syringe "Back-up Diluted LUXTURNA" using the sterile skin marker. The second syringe will serve as a backup for the surgeon performing the subretinal administration procedure. Discard the back-up syringe after surgery if not used.
20. Inspect both syringes. If particulates, cloudiness, or discoloration are visible, do not use the syringe.
21. Place the syringes into the sterile plastic bag after visual inspection and seal the bag.
22. Place the sterile plastic bag with syringes containing diluted LUXTURNA into an appropriate secondary container (e.g., hard plastic cooler) for delivery to the surgical suite at room temperature.

2.3 Administration

LUXTURNA should be administered in the surgical suite under controlled aseptic conditions by a surgeon experienced in performing intraocular surgery. In addition to the syringe containing the diluted LUXTURNA, the following items are required for administration:

- Subretinal injection cannula with a polyamide micro tip with an inner diameter of 41gauge.
- Extension tube made of polyvinyl chloride no longer than 6" (15.2 cm) in length and with an inner diameter no greater than 1.4mm.

Figure 3. Injection Apparatus Assembly

Follow the steps below for subretinal injection:

1. After confirming the availability of LUXTURNA, dilate the eye and give adequate anesthesia to the patient.
2. Administer a topical broad spectrum microbiocide to the conjunctiva, cornea and eyelids prior to surgery.
3. Inspect LUXTURNA prior to administration. If particulates, cloudiness, or discoloration are visible, do not use the product.
4. Connect the syringe containing the diluted LUXTURNA to the extension tube and subretinal injection cannula. To avoid excess priming volume, the extension tube should not exceed 15.2 cm in length and 1.4 mm in inner diameter. Inject the product slowly through the extension tube and the subretinal injection cannula to eliminate any air bubbles.
5. Confirm the volume of product available in the syringe for injection, by aligning the plunger tip with the line that marks 0.3 mL. (Figure 4)

Figure 4. Volume of LUXTURNA for Injection

6. After completing a vitrectomy, identify the intended site of administration. The subretinal injection cannula can be introduced via pars plana. (Figure 5a)
7. Under direct visualization, place the tip of the subretinal injection cannula in contact with the retinal surface. The recommended site of injection is located along the superior vascular arcade, at least 2 mm distal to the center of the fovea (Figure 5b), avoiding direct contact with the retinal vasculature or with areas of pathologic features, such as dense atrophy or intraretinal pigment migration. Inject a small amount of the product slowly until an initial subretinal bleb is observed. Then inject the remaining volume slowly until the total 0.3 mL is delivered.

Figure 5a. Subretinal Injection Cannula Introduced via Pars Plana

Figure 5b. Tip of the Subretinal Injection Cannula Placed Within the Recommended Site of Injection (Surgeon's Point of View)

8. After completing the injection, remove the subretinal injection cannula from the eye.
9. Following injection, discard all unused product. Dispose of the back-up syringe according to local biosafety guidelines applicable for handling and disposal of the product.
10. Perform a fluid-air exchange, carefully avoiding fluid drainage near the retinotomy created for the subretinal injection.
11. Initiate supine head positioning immediately in the post-operative period.
12. Upon discharge, advise patients to rest in a supine position as much as possible for 24 hours.

3 DOSAGE FORMS AND STRENGTHS

LUXTURNA is a suspension for subretinal injection, supplied in a 0.5-mL extractable volume in a 2-mL single-dose vial; the supplied concentration (5 x 10^12 vg/mL) requires a 1:10 dilution prior to administration. The Diluent is supplied in two single-use 2 mL vials.

4 CONTRAINDICATIONS

None.

5 WARNINGS AND PRECAUTIONS

5.1 Endophthalmitis

Endophthalmitis may occur following any intraocular surgical procedure or injection. Use proper aseptic injection technique when administering LUXTURNA. Following the injection, monitor patients to permit early treatment of any infection. Advise patients to report any signs or symptoms of infection or inflammation without delay.

5.2 Permanent Decline in Visual Acuity

Permanent decline in visual acuity may occur following subretinal injection of LUXTURNA. Monitor patients for visual disturbances.

5.3 Retinal Abnormalities

Retinal abnormalities may occur during or following the subretinal injection of LUXTURNA, including macular holes, foveal thinning, loss of foveal function, foveal dehiscence, chorioretinal atrophy, and retinal hemorrhage. Monitor and manage these retinal abnormalities appropriately. Do not administer LUXTURNA in the immediate vicinity of the fovea [see Dosage and Administration (2.3)].

Retinal abnormalities may occur during or following vitrectomy including retinal tears, epiretinal membrane, or retinal detachment. Monitor patients during and following the injection to permit early treatment of these retinal abnormalities. Advise patients to report any signs or symptoms of retinal tears and/or detachment without delay.

5.4 Increased Intraocular Pressure

Increased intraocular pressure may occur after subretinal injection of LUXTURNA. Monitor and manage intraocular pressure appropriately.

5.5 Expansion of Intraocular Air Bubbles

Instruct patients to avoid air travel, travel to high elevations or scuba diving until the air bubble formed following administration of LUXTURNA has completely dissipated from the eye. It may take one week or more following injection for the air bubble to dissipate. A change in altitude while the air bubble is still present can result in irreversible vision loss. Verify the dissipation of the air bubble through ophthalmic examination.

5.6 Cataract

Subretinal injection of LUXTURNA, especially vitrectomy surgery, is associated with an increased incidence of cataract development and/or progression.

6 ADVERSE REACTIONS

The most common adverse reactions (incidence ≥ 5%) were conjunctival hyperemia, cataract, increased intraocular pressure, retinal tear, dellen (thinning of the corneal stroma), macular hole, subretinal deposits, eye inflammation, eye irritation, eye pain, and maculopathy (wrinkling on the surface of the macula).

6.1 Clinical Trials Experience

Because clinical trials are conducted under widely varying conditions, adverse reaction rates observed in the clinical trials of a drug cannot be directly compared to rates in the clinical trials of other products and may not reflect the rates observed in practice.

The safety data described in this section reflect exposure to LUXTURNA in two clinical trials consisting of 41 subjects (81 eyes) with confirmed biallelic RPE65 mutation-associated retinal dystrophy. Forty of the 41 subjects received sequential subretinal injections of LUXTURNA to each eye. One subject received LUXTURNA in only one eye. Seventy-two of the 81 eyes were exposed to the recommended dose of LUXTURNA at 1.5 x 10^11 vg; 9 eyes were exposed to lower doses of LUXTURNA. Study 1 (n=12) was an open-label, dose-exploration safety study. Study 2 (n=29) was an open-label, randomized, controlled study for both efficacy and safety [see Clinical Studies (14)]. The average age of the 41 subjects was 17 years, ranging from 4 to 44 years. Of the 41 subjects, 25 (61%) were pediatric subjects under 18 years of age, and 23 (56%) were females.

Twenty-seven (27/41, 66%) subjects had ocular adverse reactions that involved 46 injected eyes (46/81, 57%). Adverse reactions among all subjects in Studies 1 and 2 are described in Table 1. Adverse reactions may have been related to voretigene neparvovec-rzyl, the subretinal injection procedure, the concomitant use of corticosteroids, or a combination of these procedures and products.

Table 1. Ocular Adverse Reactions Following Treatment with LUXTURNA (N=41)
Adverse Reactions | Subjects n=41 | Treated Eyes n=81
Any ocular adverse reaction | 27 (66%) | 46 (57%)
Conjunctival hyperemia | 9 (22%) | 9 (11%)
Cataract | 8 (20%) | 15 (19%)
Increased intraocular pressure | 6 (15%) | 8 (10%)
Retinal tear | 4 (10%) | 4 (5%)
Dellen (thinning of the corneal stroma) | 3 (7%) | 3 (4%)
Macular hole | 3 (7%) | 3 (4%)
Subretinal deposits* | 3 (7%) | 3 (4%)
Eye inflammation | 2 (5%) | 4 (5%)
Eye irritation | 2 (5%) | 2 (2%)
Eye pain | 2 (5%) | 2 (2%)
Maculopathy (wrinkling on the surface of the macula) | 2 (5%) | 3 (4%)
Foveal thinning and loss of foveal function | 1 (2%) | 2 (2%)
Endophthalmitis | 1 (2%) | 1 (1%)
Foveal dehiscence (separation of the retinal layers in the center of the macula) | 1 (2%) | 1 (1%)
Retinal hemorrhage | 1 (2%) | 1 (1%)

*Transient appearance of asymptomatic subretinal precipitates inferior to the retinal injection site 1-6 days after injection

Immunogenicity

At all doses of LUXTURNA evaluated in Studies 1 and 2, immune reactions and extra-ocular exposure were mild. In Study 1 (n=12), the interval between the subretinal injections into the two eyes ranged from 1.7 to 4.6 years. In Study 2, the interval between the subretinal injections into the two eyes ranged from 7 to 14 days. No subject had a clinically significant cytotoxic T-cell response to either AAV2 or RPE65.

Subjects received systemic corticosteroids before and after subretinal injection of LUXTURNA to each eye. The corticosteroids may have decreased the potential immune reaction to either vector capsid (adeno-associated virus serotype 2 [AAV2] vector) or transgene product (retinoid isomerohydrolase RPE65 [RPE65]).

6.2 Postmarketing Experience

The following adverse reactions have been identified during postapproval use of LUXTURNA. Because these reactions are reported voluntarily, it is not always possible to reliably estimate their frequency or establish a causal relationship to drug exposure.

Eye Disorders: chorioretinal atrophy (also reported as retinal degeneration, retinal depigmentation, and injection site atrophy).

8 USE IN SPECIFIC POPULATIONS

8.1 Pregnancy

Risk Summary

Adequate and well-controlled studies with LUXTURNA have not been conducted in pregnant women. Animal reproductive studies have not been conducted with LUXTURNA. In the U.S. general population, the estimated background risk of major birth defects and miscarriage in clinically recognized pregnancies is 2-4% and 15-20%, respectively.

8.2 Lactation

Risk Summary

There is no information regarding the presence of LUXTURNA in human milk, the effects on the breastfed infant, or the effects on milk production. The developmental and health benefits of breastfeeding should be considered along with the mother's clinical need for LUXTURNA and any potential adverse effects on the breastfed infant from LUXTURNA.

8.3 Females and Males of Reproductive Potential

No nonclinical or clinical studies were performed to evaluate the effect of LUXTURNA on fertility.

8.4 Pediatric Use

Treatment with LUXTURNA is not recommended for patients younger than 12 months of age, because the retinal cells are still undergoing cell proliferation, and LUXTURNA would potentially be diluted or lost during cell proliferation.

The safety and efficacy of LUXTURNA have been established in pediatric patients. Use of LUXTURNA is supported by Study 1 and Study 2 [see Clinical Studies (14)] that included 25 pediatric patients with biallelic RPE65 mutation-associated retinal dystrophy in the following age groups: 21 children (age 4 years to less than 12 years) and 4 adolescents (age 12 years to less than 17 years). There were no significant differences in safety between the different age subgroups.

8.5 Geriatric Use

The safety and effectiveness of LUXTURNA have not been established in geriatric patients. Clinical studies of LUXTURNA for this indication did not include patients age 65 years and over.

11 DESCRIPTION

LUXTURNA (voretigene neparvovec-rzyl) is a suspension of an adeno-associated virus vector-based gene therapy for subretinal injection. LUXTURNA is a live, non-replicating adeno-associated virus serotype 2 which has been genetically modified to express the human RPE65 gene. LUXTURNA is derived from naturally occurring adeno-associated virus using recombinant DNA techniques.

Each single-dose vial of LUXTURNA contains 5 x 10^12 vector genomes (vg) per mL, and the excipients 180 mM sodium chloride, 10 mM sodium phosphate, and 0.001% Poloxamer 188 (pH 7.3), in a 0.5-mL extractable volume. LUXTURNA requires a 1:10 dilution prior to administration. After dilution, each dose of LUXTURNA consists of 1.5 x 10^11 vg in a deliverable volume of 0.3 mL.

The Diluent, supplied in 1.7 mL extractable volume per vial in two 2-mL vials, is composed of sterile water containing 180 mM sodium chloride, 10 mM sodium phosphate, and 0.001% Poloxamer 188 (pH 7.3).

LUXTURNA may also contain residual components of HEK293 cells including DNA and protein and trace quantities of fetal bovine serum.

The product contains no preservative.

12 CLINICAL PHARMACOLOGY

12.1 Mechanism of Action

LUXTURNA is designed to deliver a normal copy of the gene encoding the human retinoid isomerohydrolase RPE65 (RPE65) to cells of the retina in persons with reduced or absent levels of biologically active RPE65. The RPE65 is produced in the retinal pigment epithelial (RPE) cells and converts all-trans-retinol to 11-cis-retinol, which subsequently forms the chromophore, 11-cis-retinal, during the visual (retinoid) cycle. The visual cycle is critical in phototransduction, which refers to the biological conversion of a photon of light into an electrical signal in the retina. Mutations in the RPE65 gene lead to reduced or absent levels of retinoid isomerohydrolase RPE65 activity, blocking the visual cycle and resulting in impairment of vision.

12.2 Pharmacodynamics

Injection of LUXTURNA into the subretinal space results in transduction of some retinal pigment epithelial cells with a cDNA encoding normal human RPE65 protein, thus providing the potential to restore the visual cycle.

12.3 Pharmacokinetics

Biodistribution (within the body) and Vector Shedding (excretion/secretion)

LUXTURNA vector DNA levels in various tissues and secretions were determined using a quantitative polymerase chain reaction (qPCR) assay.

Nonclinical data

Biodistribution of LUXTURNA was evaluated at three months following subretinal administration in non-human primates. The highest levels of vector DNA sequences were detected in intraocular fluids (anterior chamber fluid and vitreous) of vector-injected eyes. Low levels of vector DNA sequences were detected in the optic nerve of the vector-injected eye, optic chiasm, spleen and liver, and sporadically in the lymph nodes. Vector DNA sequences were not detected in the gonads.

Clinical data

LUXTURNA vector shedding and biodistribution were investigated in a study measuring LUXTURNA DNA in tears from both eyes, and from serum, and whole blood of subjects in Study 2. In summary, LUXTURNA vector was shed transiently and at low levels in tears from the injected eye in 45% of the subjects in Study 2, and occasionally (7%) from the uninjected eye until Day 3 post-injection.

In 29 subjects who received bilateral administrations, LUXTURNA vector DNA was present in tear samples of 13 subjects (45%). Peak levels of vector DNA were detected in the tear samples on Day 1 post-injection, after which no vector DNA was detected in a majority of the subjects (8 of 13). Three subjects (10%) had vector DNA in tear samples until Day 3 post-injection, and two subjects (7%) had vector DNA in tear samples for around two weeks post-injection. In another two subjects (7%), vector DNA was detected in tear samples from the uninjected (or previously injected) eye until Day 3 post-injection. Vector DNA was detected in serum in 3/29 (10%) subjects, including two with vector DNA in tear samples up to Day 3 following each injection.

Specific Populations

No pharmacokinetic studies with LUXTURNA have been conducted.

Drug Interaction Studies

No interaction studies have been performed with LUXTURNA.

13 NONCLINICAL TOXICOLOGY

13.1 Carcinogenesis, Mutagenesis, Impairment of Fertility

No animal studies have been conducted to evaluate the effects of LUXTURNA on carcinogenesis, mutagenesis, and impairment of fertility.

13.2 Animal Toxicology and/or Pharmacology

Bilateral, simultaneous subretinal administration of LUXTURNA was well tolerated at dose levels up to 8.25 x 10^10 vg per eye in dogs with a naturally occurring RPE-65 mutation and 7.5 x 10^11 vg (5 times higher than the recommended human dose level) per eye in non-human primates (NHPs) with normal-sighted eyes. In both animal models, bilateral, sequential subretinal administrations, where the contralateral eye was injected following the first eye, were well tolerated at the recommended human dose level of 1.5 x 10^11 vg per eye. In addition, dogs with the RPE-65 mutation displayed improved visual behavior and pupillary responses. Ocular histopathology showed only mild changes, which were mostly related to healing from the surgical administration procedure. Other findings observed following subretinal injection of LUXTURNA in dogs and NHPs included occasional and isolated inflammatory cells in the retina, with no apparent retinal degeneration. Dogs not previously exposed to AAV2 vectors developed antibodies to the AAV2 capsid following a single administration of LUXTURNA, whereas NHPs did not.

14 CLINICAL STUDIES

The efficacy of LUXTURNA in pediatric and adult patients with biallelic RPE65 mutation-associated retinal dystrophy was evaluated in an open-label, two-center, randomized trial (Study 2). Of the 31 enrolled subjects, 21 subjects were randomized to receive subretinal injection of LUXTURNA. One subject discontinued from the study prior to treatment. Ten subjects were randomized to the control (non-intervention) group. One subject in the control group withdrew consent and was discontinued from the study. The nine subjects who were randomized to the control group were crossed over to receive subretinal injection of LUXTURNA after one year of observation. The average age of the 31 randomized subjects was 15 years (range 4 to 44 years), including 64% pediatric subjects (n=20, age from 4 to 17 years) and 36% adults (n=11). The 31 randomized subjects included 13 males and 18 females. Sixty-eight percent (68%) of the subjects were White, 16% were Asian, 10% were American Indian or Alaska Native, and 6% were Black or African-American. Bilateral subretinal injections of LUXTURNA were administered sequentially in two separate surgical procedures with an interval of 6 to 18 days.

The efficacy of LUXTURNA was established on the basis of multi-luminance mobility testing (MLMT) score change from Baseline to Year 1. The MLMT was designed to measure changes in functional vision, as assessed by the ability of a subject to navigate a course accurately and at a reasonable pace at different levels of environmental illumination. The MLMT was assessed using both eyes and each eye separately at one or more of seven levels of illumination, ranging from 400 lux (corresponding to a brightly lit office) to 1 lux (corresponding to a moonless summer night). Each light level was assigned a score code ranging from 0 to 6. A higher score indicated that a subject was able to pass the MLMT at a lower light level. A score of -1 was assigned to subjects who could not pass MLMT at a light level of 400 lux. The MLMT of each subject was videotaped and assessed by independent graders. The MLMT score was determined by the lowest light level at which the subject was able to pass the MLMT. The MLMT score change was defined as the difference between the score at Baseline and the score at Year 1. A positive MLMT score change from Baseline to Year 1 visit indicated that the subject was able to complete the MLMT at a lower light level.

Additional clinical outcomes were also evaluated, including full-field light sensitivity threshold (FST) testing, visual acuity, and visual fields.

Table 2 summarizes the median MLMT score change from Baseline to Year 1 in the LUXTURNA treatment group as compared to the control group. A median MLMT score change of 2 was observed in the LUXTURNA treatment group, while a median MLMT score change of 0 was observed in the control group, when using both eyes or the first-treated eye. An MLMT score change of two or greater is considered a clinically meaningful benefit in functional vision.

Table 2. Efficacy Results of Study 2 at Year 1, Compared to Baseline
Efficacy Outcomes | LUXTURNA n=21 | Control n=10 | Difference (LUXTURNA minus Control) | p-value
MLMT score change for bilateral eyes, median (min, max) | 2 (0, 4) | 0 (-1, 2) | 2 | 0.001
MLMT score change for first-treated eye, median (min, max) | 2 (0, 4) | 0 (-1, 1) | 2 | 0.003

Table 3 shows the number and percentage of subjects with different magnitudes of MLMT score change using both eyes at Year 1. Eleven of the 21 (52%) subjects in the LUXTURNA treatment group had an MLMT score change of two or greater, while one of the ten (10%) subjects in the control group had an MLMT score change of two.

Table 3. Magnitude of MLMT Score Change Using Both Eyes at Year 1 (Study 2)
Score Change | LUXTURNA n=21 | Control n=10
-1 | 0 | 3 (30%)
0 | 2 (10%) | 3 (30%)
1 | 8 (38%) | 3 (30%)
2 | 5 (24%) | 1 (10%)
3 | 5 (24%) | 0
4 | 1 (4%) | 0

Figure 6 shows MLMT performance of individual subjects using both eyes at Baseline and at Year 1.

Figure 6. MLMT Score Using Both Eyes at Baseline and Year 1 for Individual Subjects (Study 2)

Note for Figure 6: *subjects who were withdrawn or discontinued. The open circles are the baseline scores. The closed circles are the Year 1 scores. The numbers next to the solid circle represent score change at Year 1. The horizontal lines with arrows represent the magnitude of the score change and its direction. Arrows pointing towards the right represent improvement. The top section shows the results of the 21 subjects in the treatment group. The bottom section shows the results of the 10 subjects in the control group. Subjects in each group are chronologically organized by age, with the youngest subject at the top and the oldest subject at the bottom.

Analysis of white light FST testing showed statistically significant improvement from Baseline to Year 1 in the LUXTURNA treatment group compared to the control group. The change in visual acuity from Baseline to Year 1 was not significantly different between the LUXTURNA and control groups.

Figure 7 shows the effect of LUXTURNA over the two-year period in the LUXTURNA treatment group, as well as the effect in the control group after crossing over to receive subretinal injection of LUXTURNA. A median MLMT score change of two was observed for the LUXTURNA treatment group at Day 30, and this effect was sustained over the remaining follow-up visits throughout the two-year period. For the control group, a median MLMT score change of 0 was observed at all four follow up visits during the first year. However, after crossing-over to receive subretinal injection of LUXTURNA, the subjects in the control group showed a similar response to LUXTURNA as compared to the subjects in the LUXTURNA treatment group.

Figure 7. MLMT Time-Course over Two Years: Using Both Eyes (Study 2)

Note for Figure 7: Each box represents the middle 50% of distribution of MLMT score change. Vertical dotted lines represent additional 25% above and below the box. The horizontal bar within each box represents the median. The dot within each box represents the mean. The solid line connects the mean MLMT score changes over visits for the treatment group, including five visits during the first year and one visit at Year 2 (marked as x365). The dotted line connects the mean MLMT score change over visits for the control group, including five visits during the first year without receiving LUXTURNA, and four visits within the second year (marked as x30, x90, x180, and x365) after cross-over at Year 1 to receive LUXTURNA.

16 HOW SUPPLIED/STORAGE AND HANDLING

Each carton of LUXTURNA (NDC 71394 – 415-01) contains one single-dose vial of the LUXTURNA (NDC 71394 – 065-01, 0.5 mL extractable volume) and two vials of Diluent (NDC 71394 – 716-01, 1.7 mL extractable volume in each vial). LUXTURNA contains 5 x 10^12 vector genomes (vg) per mL and requires a 1:10 dilution prior to administration.

Store LUXTURNA and Diluent frozen at ≤ -65 °C.

Following thaw of the vials, store at room temperature. Store diluted LUXTURNA at room temperature [See Dosage and Administration 2.2].

LUXTURNA is an adeno-associated virus vector-based gene therapy. Follow universal biohazard precautions for handling.

17 PATIENT COUNSELING INFORMATION

Advise patients and/or their caregivers of the following risks:

- Endophthalmitis and other eye infections

Serious infection can occur inside of the eye and may lead to blindness. In such cases, there is an urgent need for management without delay. Advise patients to call their healthcare provider if they experience new floaters, eye pain, or any change in vision.

- Permanent decline in visual acuity

Permanent decline in visual acuity may occur following subretinal injection of LUXTURNA. Advise patients to contact their healthcare provider if they experience any change in vision.

- Retinal abnormalities

Treatment with LUXTURNA may cause some defects in the retina such as a small tear or a hole in the area or vicinity of the injection. Treatment may cause thinning of the central retina, loss of retinal cells and the choroid (layer of blood vessels that line the back of the eye), or bleeding in the retina. Advise patients to follow up with their healthcare provider on a regular basis and report any symptoms such as decreased vision, blurred vision, flashes of light, or floaters in their vision without delay.

- Increased intraocular pressure

Treatment with LUXTURNA may cause transient or persistent increase in intraocular pressure. If untreated, such increases in intraocular pressure may cause blindness. Advise patients to follow-up with their healthcare provider to detect and treat any increase in intraocular pressure.

- Expansion of intraocular air bubbles

Advise patients to avoid air travel, travel to high elevations, or scuba diving until the air bubble formed following administration of LUXTURNA has completely dissipated from the eye. A change in altitude while the air bubble is still present may cause irreversible damage.

- Cataract

Advise patients that following treatment with LUXTURNA, they may develop a new cataract, or any existing cataract may get worse.

- Shedding of LUXTURNA

Transient and low level shedding of LUXTURNA may occur in patient tears. Advise patients and/or their caregivers on proper handling of waste material generated from dressing, tears, and nasal secretion, which may include storage of waste material in sealed bags prior to disposal. These handling precautions should be followed for up to 7 days following LUXTURNA administration.

Manufactured by:
Spark Therapeutics, Inc.
3737 Market Street
Philadelphia, PA 19104

US License #2056

Principal Display Panel - Luxturna Carton Label

NDC 71394-415-01

Rx only

voretigene neparvovec-rzyl

LUXTURNA™

5 x 10^12 vector genomes/mL. No US standard of potency.
One (1) single-dose vial of voretigene neparvovec-rzyl, 0.5 mL per vial
Two (2) vials of Diluent for voretigene neparvovec-rzyl, 1.7 mL per vial
Store at ≤ -65°C. Dilute before use. Discard unused portion.
For administration by subretinal injection
See package insert for full prescribing information and instructions for
dosage and administration.

Manufactured by Spark Therapeutics Inc.
3737 Market Street, Suite 1300
Philadelphia, Pennsylvania 19104
US License No. 2056

Principal Display Panel - Diluent for Voretigene Neparvovec Label

NDC 71394-716-01

Diluent for voretigene neparvovec-rzyl
pH 7.3, containing 0.001%
poloxamer 188
For Rx only
1.7 mL per vial; Store at ≤ -65 °C
Manufactured for Spark Therapeutics
By Nova Laboratories
US License No. 2056

Principal Display Panel - Luxturna Label

NDC 71394-065-01

voretigene neparvovec-rzyl
For subretinal injection

5 x 10^12 vector genomes/mL
One (1) single-dose vial, 0.5 mL per vial
For Rx only; Must dilute before use
Store at ≤ -65 °C; Discard unused portion
Manufactured by
Spark Therapeutics, Inc.
US License No. 2056

Principal Display Panel - Luxturna Pouch Label

NDC 71394-415-01

Rx only

voretigene neparvovec-rzyl

LUXTURNA™

5 x 10^12 vector genomes/mL. No US standard of potency.

One (1) single-dose vial of voretigene neparvovec-rzyl, 0.5 mL per vial
Two (2) vials of Diluent for voretigene neparvovec-rzyl, 1.7 mL per vial
Store at ≤ -65 °C. Dilute before use. Discard unused portion.
For administration by subretinal injection
See package insert for full prescribing information and instructions
for dosage and administration

NDC 71394-415-01

Manufactured by Spark Therapeutics
3737 Market Street, Suite 1300
Philadelphia, Pennsylvania 19104
US License No. 2056